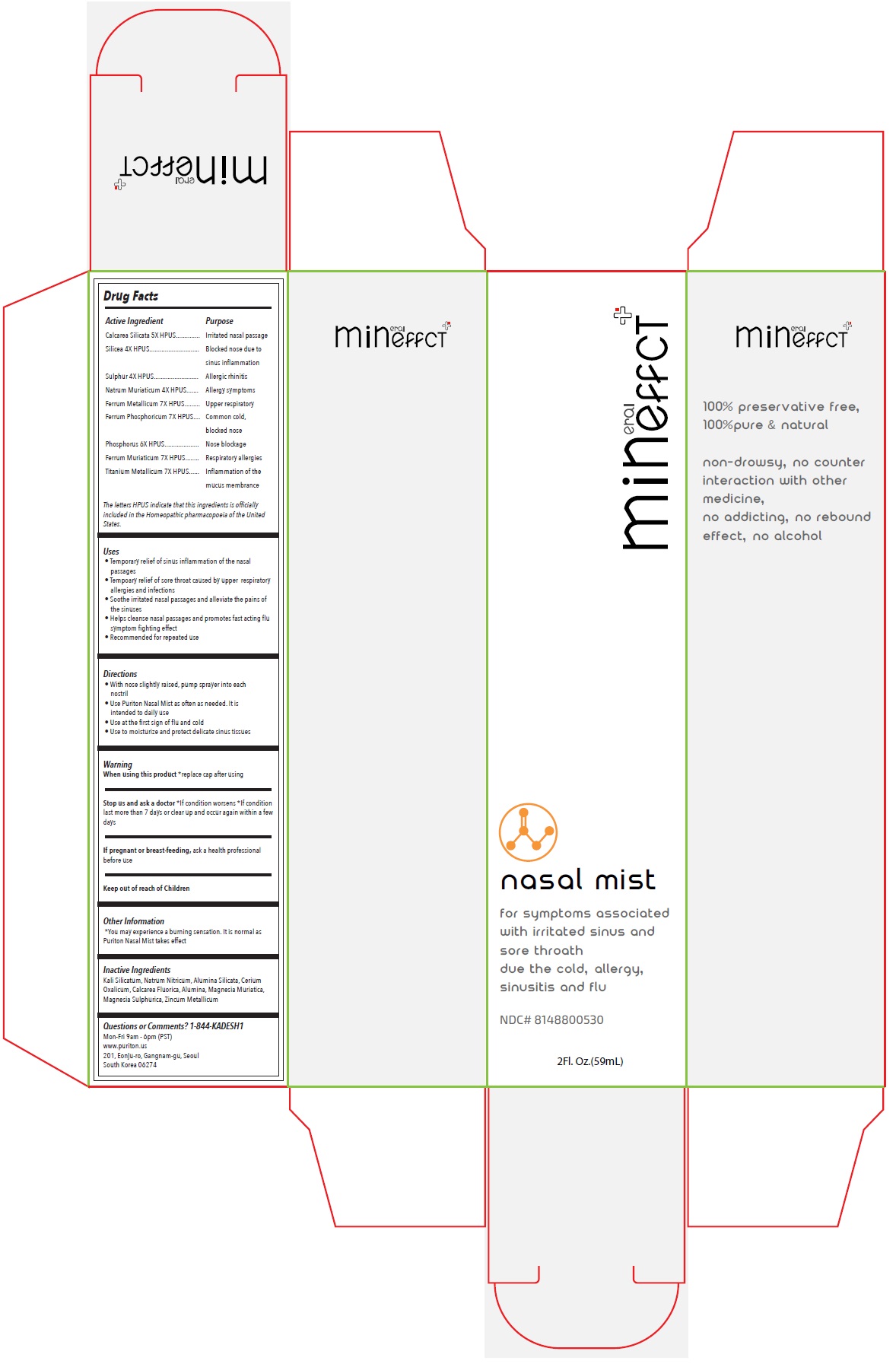 DRUG LABEL: Mineffect nasal mist
NDC: 81488-005 | Form: SPRAY
Manufacturer: Kadesh Incoporation Co,Ltd
Category: homeopathic | Type: HUMAN OTC DRUG LABEL
Date: 20231031

ACTIVE INGREDIENTS: CALCIUM SILICATE 5 [hp_X]/59 mL; SILICON DIOXIDE 4 [hp_X]/59 mL; SULFUR 4 [hp_X]/59 mL; SODIUM CHLORIDE 4 [hp_X]/59 mL; IRON 7 [hp_X]/59 mL; FERROSOFERRIC PHOSPHATE 7 [hp_X]/59 mL; PHOSPHORUS 6 [hp_X]/59 mL; FERRIC CHLORIDE HEXAHYDRATE 7 [hp_X]/59 mL; TITANIUM 7 [hp_X]/59 mL
INACTIVE INGREDIENTS: POTASSIUM SILICATE; SODIUM NITRATE; KAOLIN; CEROUS OXALATE NONAHYDRATE; CALCIUM FLUORIDE; ALUMINUM OXIDE; MAGNESIUM CHLORIDE; MAGNESIUM SULFATE HEPTAHYDRATE; ZINC

Mineffect nasal mist

Active Ingredient

Calcarea Silicata 5X HPUS

Silicea 4X HPUS

Sulphur 4X HPUS

Natrum Muriaticum 4X HPUS

Ferrum Metallicum 7X HPUS

Ferrum Phosphoricum 7X HPUS

Phosphorus 6X HPUS

Ferrum Muriaticum 7X HPUS

Titanium Metallicum 7X HPUS

The letters HPUS indicate that this ingredients is officially included in the Homeopathic pharmacopoeia of the United States.

Purpose

Irritated nasal passage

Blocked nose due to sinus inflammation

Allergic rhinitis

Allergy symptoms

Upper respiratory

Common cold, blocked nose

Nose blockage

Respiratory allergies

Inflammation of the mucus membrane

Uses

• Temporary relief of sinus inflammation of the nasal passages

• Temporary relief of sore throat caused by upper respiratory allergies and infections

• Soothe irritated nasal passages and alleviate the pains of the sinuses

• Helps cleanse nasal passages and promotes fast acting flu symptom fighting effect

• Recommended for repeated use

Directions

• With nose slightly raised, pump sprayer into each nostril

• Use Puriton Nasal Mist as often as needed. It is intended to daily use

• Use at the first sign of flu and cold

• Use to moisturize and protect delicate sinus tissues

Warning

When using this product*replace cap after using

Stop use and ask a doctor*If condition worsens *If condition last more than 7 days or clear up and occur again within a few days

If pregnant or breast-feeding,ask a health professional before use

Keep out of reach of Children

Other Information

*You may experience a burning sensation. It is normal as Puriton Nasal Mist takes effect

Inactive Ingredients

Kali Silicatum, Natrum Nitricum, Alumina Silicata, Cerium Oxalicum, Calcarea Fluorica, Alumina, Magnesia Muriatica, Magnesia Sulphurica, Zincum Metallicum

Questions or Comments? 1-844-KADESH1

Mon-Fri 9am - 6pm (PST)

www.puriton.us

201, Eonju-ro, Gangnam-gu, Seoul

South Korea 06274

for symptoms associated with irritated sinus and sore throat due the cold, allergy, sinusitis and flu

100% preservative free,

100% pure & natural

non-drowsy, no counter interaction with other medicine,

no addicting, no rebound effect, no alcohol